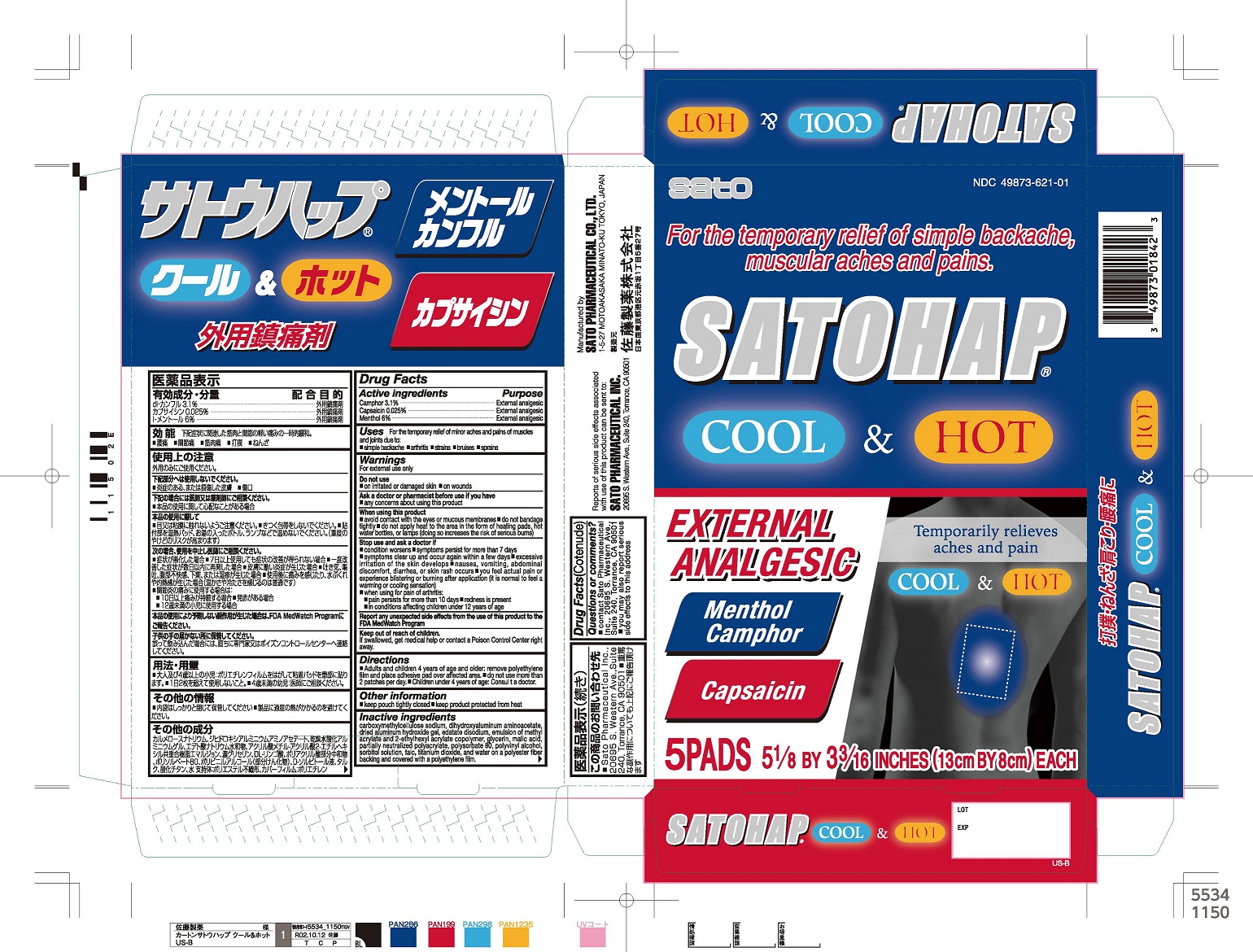 DRUG LABEL: Satohap Cool and Hot Pads
NDC: 49873-621 | Form: PATCH
Manufacturer: Sato Pharmaceutical Co., Ltd.
Category: otc | Type: HUMAN OTC DRUG LABEL
Date: 20240901

ACTIVE INGREDIENTS: CAMPHOR (SYNTHETIC) 3.1 g/100 g; LEVOMENTHOL 6 g/100 g; CAPSAICIN 0.025 g/100 g
INACTIVE INGREDIENTS: ACRYLIC ACID/SODIUM ACRYLATE COPOLYMER (1:1; 600 MPA.S AT 0.2%); 2-ETHYLHEXYL ACRYLATE; METHYL ACRYLATE; POLYSORBATE 80; CARBOXYMETHYLCELLULOSE SODIUM; SORBITOL; TITANIUM DIOXIDE; ALUMINUM HYDROXIDE; DIHYDROXYALUMINUM AMINOACETATE; WATER; MALIC ACID; POLYVINYL ALCOHOL, UNSPECIFIED; GLYCERIN; TALC; EDETATE DISODIUM

Satohap Cool & Hot Pads - 5 pads in 1 pouch - (13cm by 8cm each pad)

Active ingredients

Camphor 3.1%

Capsaicin 0.025%

Menthol 6%

Purpose

External analgesic

External analgesic

External analgesic

Uses

For the temporary relief of minor aches and pains of muscles and joints due to:

- simple backache
- arthritis
- strains
- bruises
- sprains

Warnings

For external use only

Do not use

- on irritated or damaged skin
- on wounds

Ask a doctor or pharmacist before use if you have

- any concerns about using this product

When using this product

- avoid contact with the eyes or mucus membranes
- do not bandage tightly
- do not apply heat to the area in the form of heating pads, hot water bottles, or lamps (doing so increases the risk of serious burns)

Stop use and ask a doctor if

- condition worsens
- symptoms persist for more than 7 days
- symptoms clear up and occur again within a few days
- excessive irritation of the skin develops
- nausea, vomiting, abdominal discomfort, diarrhea, or skin rash occurs.
- you feel actual pain or experience blistering or burning after application (it is normal to feel a warming or cooling sensation)
- when using for pain or arthritis:
- pain persists for more than 10 days
- redness is present
- in conditions affecting children under 12 years of age

Keep out of reach of children.

If swallowed, get medical help or contact a Poison Control Center right away.

Directions

- Adults and children 4 years of age and older: remove polyethylene film and place adhesive pad over affected area.
- do not use more than 2 patches per day.
- Children under 4 years of age: Consult a doctor.

Other information

- keep pouch tightly closed
- keep product protected from heat

Inactive ingredients

carboxymethylcellulose sodium, dihydroxyaluminum aminoacetate, dried aluminum hydroxide gel, edetate disodium, emulsion of methyl acrylate and 2-ethylhexyl acrylate copolymer, glycerin, malic acid, partially neutralized polyacrylate, polysorbate 80, polyvinyl alcohol, sorbitol solution, talc, titanium dioxide, and water on a polyester fiber backing and covered with a polyethylene film.

Questions or comments?

- contact Sato Pharmaceutical Inc. 20695 S. Western Ave., Suite 240, Torrence, CA 90501
- you may also report serious side effects to this address